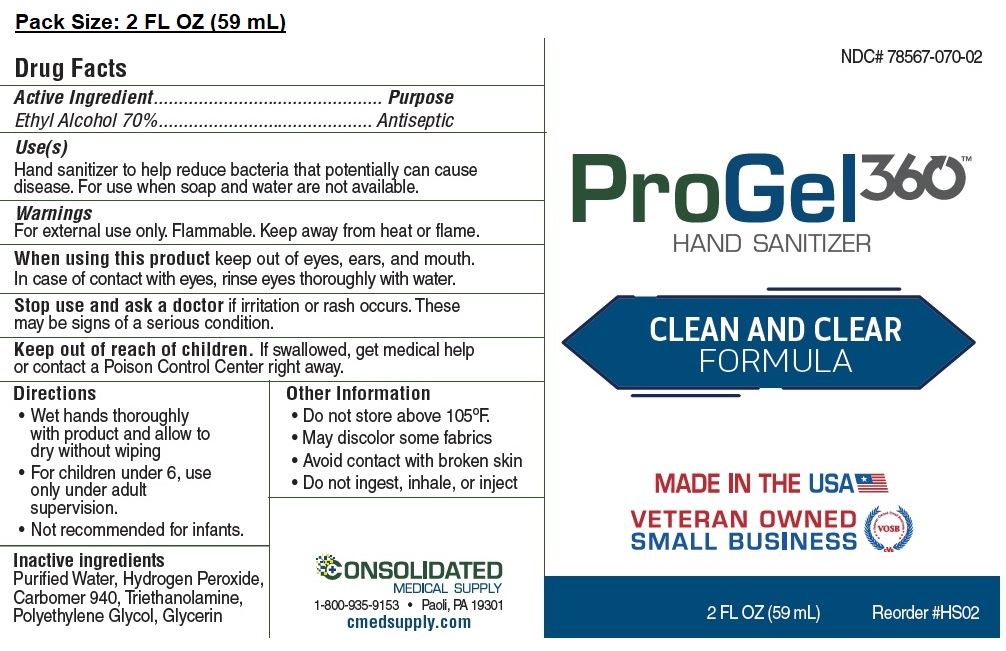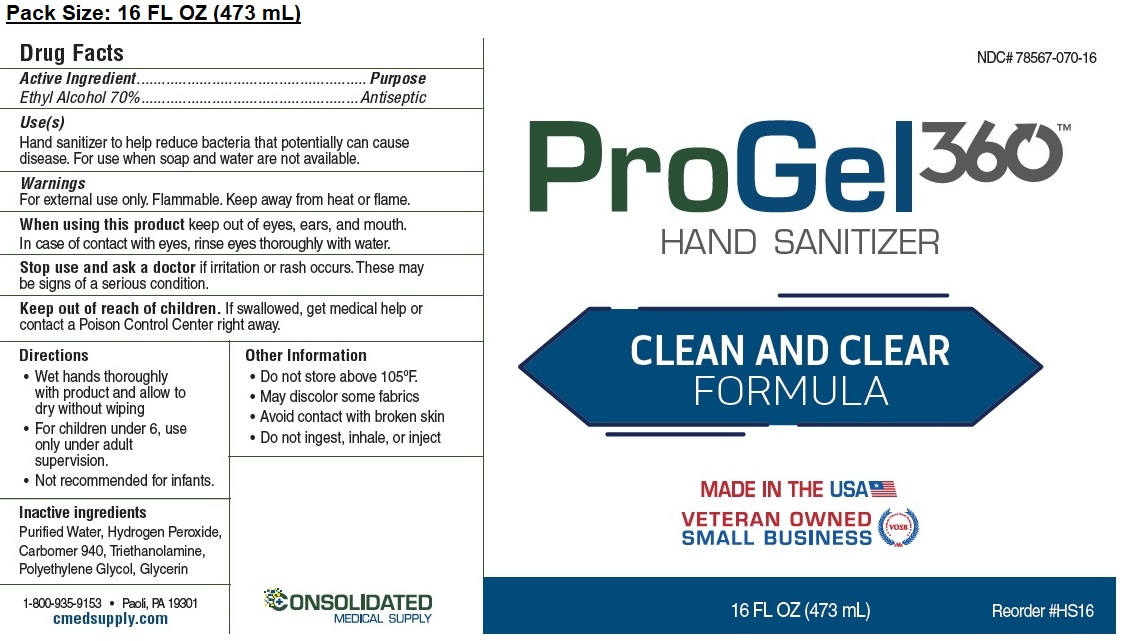 DRUG LABEL: ProGel360 Hand Sanitizer
NDC: 78567-070 | Form: GEL
Manufacturer: Steltz Pharmacy, Inc. d/b/a Consolidated Medical Supply
Category: otc | Type: HUMAN OTC DRUG LABEL
Date: 20200622

ACTIVE INGREDIENTS: ALCOHOL 70 mL/100 mL
INACTIVE INGREDIENTS: WATER; HYDROGEN PEROXIDE; CARBOMER HOMOPOLYMER TYPE C (ALLYL PENTAERYTHRITOL CROSSLINKED); TROLAMINE; POLYETHYLENE GLYCOL, UNSPECIFIED; GLYCERIN

ProGel360 Hand Sanitizer

Active Ingredient

Ethyl Alcohol 70%

Purpose

Antiseptic

Use(s)

Hand sanitizer to help reduce bacteria that potentially can cause disease. For use when soap and water are not available.

Warnings

For external use only. Flammable. Keep away from heat or flame.

When using this product keep out of eyes, ears, and mouth. In case of contact with eyes, rinse eyes thoroughly with water.

Stop use and ask a doctor if irritation or rash occurs. These may be signs of a serious condition.

Keep out of reach of children. If swallowed, get medical help or contact a Poison Control Center right away.

Directions

• Wet hands thoroughly with product and allow to dry without wiping

• For children under 6, use only under adult supervision.

• Not recommended for infants.

Other Information

• Do not store above 105ºF.

• May discolor some fabrics

• Avoid contact with broken skin

• Do not ingest, inhale, or inject

Inactive ingredients

Purified Water, Hydrogen Peroxide, Carbomer 940, Triethanolamine, Polyethylene Glycol, Glycerin

CLEAN AND CLEAR FORMULA

MADE IN THE USA

VETERAN OWNED SMALL BUSINESS

CONSOLIDATED MEDICAL SUPPLY

1-800-935-9153 • Paoli, PA 19301

cmedsupply.com